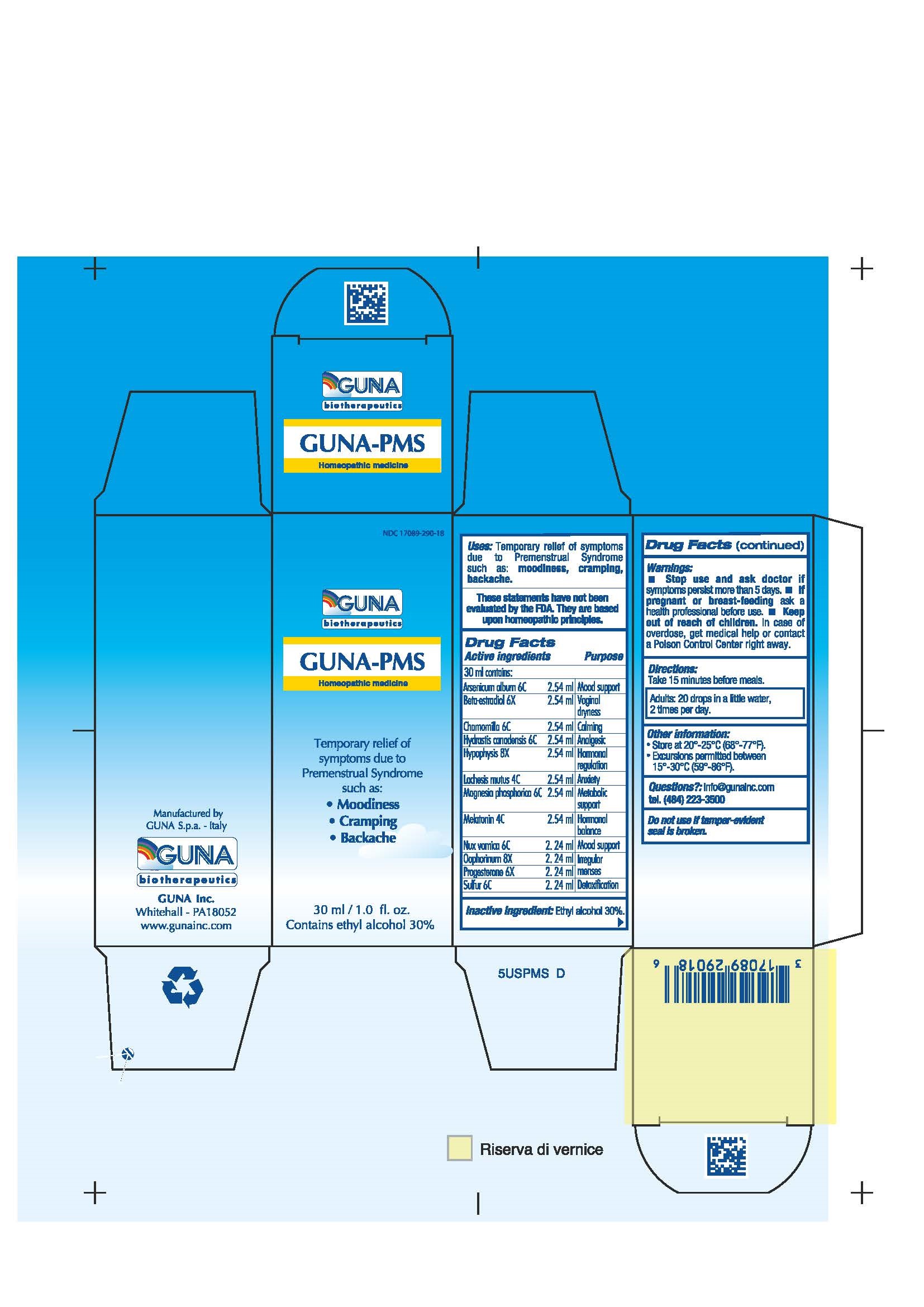 DRUG LABEL: GUNA-PMS
NDC: 17089-290 | Form: SOLUTION/ DROPS
Manufacturer: Guna spa
Category: homeopathic | Type: HUMAN OTC DRUG LABEL
Date: 20181221

ACTIVE INGREDIENTS: ARSENIC TRIOXIDE 6 [hp_C]/30 mL; ESTRADIOL 6 [hp_X]/30 mL; GOLDENSEAL 6 [hp_C]/30 mL; LACHESIS MUTA VENOM 4 [hp_C]/30 mL; MAGNESIUM PHOSPHATE, TRIBASIC, PENTAHYDRATE 6 [hp_C]/30 mL; MATRICARIA RECUTITA 6 [hp_C]/30 mL; MELATONIN 4 [hp_C]/30 mL; PROGESTERONE 6 [hp_X]/30 mL; STRYCHNOS NUX-VOMICA SEED 6 [hp_C]/30 mL; SULFUR 6 [hp_C]/30 mL; SUS SCROFA OVARY 8 [hp_X]/30 mL; SUS SCROFA PITUITARY GLAND 8 [hp_X]/30 mL
INACTIVE INGREDIENTS: ALCOHOL 9 mL/30 mL

GUNA-PMS

ACTIVE INGREDIENTS/PURPOSE

ARSENICUM ALBUM 6C MOOD SUPPORT
BETA-ESTRADIOL 6X VAGINAL DRYNESS
CHAMOMILLA 6C CALMING
HYDRASTIS CANADENSIS 6C ANALGESIC
HYPOPHYSIS 8X HORMONAL REGULATION
LACHESIS MUTUS 4C ANXIETY
MAGNESIA PHOSPHORICA 6C METABOLIC SUPPORT
MELATONIN 4C HORMONAL BALANCE
NUX VOMICA 6C MOOD SUPPORT
OOPHORINUM 8X IRREGULAR MENSES
PROGESTERONE 6X IRREGULAR MENSES
SULFUR 6C DETOXIFICATION

USES

Temporary relief of symptoms due to Premenstrual Syndrome such as:

- Moodiness
- Cramping
- Backache

PREGNANCY

If pregnant or breast-feeding ask a doctor before use

WARNINGS

Stop use and ask doctor if symptoms persist more than 5 days.
If pregnant or breast-feeding ask a health professional before use.
Keep out of reach of children. In case of overdose, get medical help or contact a Poison Control Center right away.
Contains ethyl alcohol 30%

DIRECTIONS

Adults: 20 drops in a little water, 2 times per day.

QUESTIONS

Questions?: info@gunainc.com, tel. (484) 223-3500

KEEP OUT OF REACH OF CHILDREN

INDICATIONS AND USAGE

Take 15 minutes before meals

Inactive ingredient: Ethyal alcohol 30%.